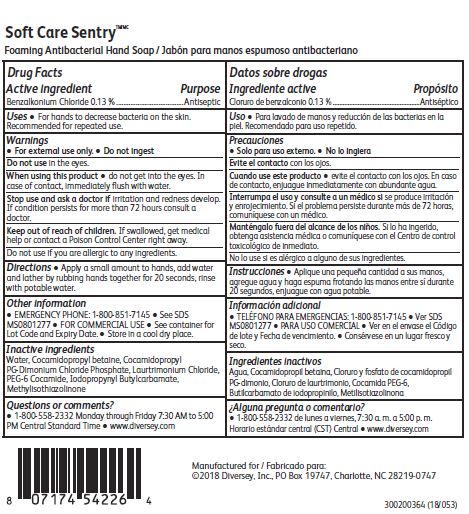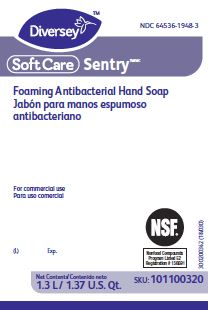 DRUG LABEL: Soft Care Sentry
NDC: 64536-1948 | Form: SOLUTION
Manufacturer: Diversey, Inc.
Category: otc | Type: HUMAN OTC DRUG LABEL
Date: 20180301

ACTIVE INGREDIENTS: BENZALKONIUM CHLORIDE 0.13 g/100 mL
INACTIVE INGREDIENTS: WATER; COCAMIDOPROPYL BETAINE; COCAMIDOPROPYL PROPYLENE GLYCOL-DIMONIUM CHLORIDE; LAURTRIMONIUM CHLORIDE; PEG-6 COCAMIDE; IODOPROPYNYL BUTYLCARBAMATE ; METHYLISOTHIAZOLINONE

Drug Facts

Active ingredient

Benzalkonium Chloride 0.13%

Purpose

Antiseptic

Uses

For hands to decrease bacteria on the skin.

Recommended for repeated use.

Warnings

For external use only.

Do not ingest

Do not use in the eyes.

When using this product do not get in eyes.

In case of contact, immediately flush with water.

Stop use and ask a doctor if irritation and redness develop.

If condition persists for more than 72 hours consult a doctor.

Keep out of reach of children.

If swallowed, get medical help or contact a Poison Control Center right away.

Do not use if you are allergic to any ingredients.

Directions

Apply a small amount to hands, add water and lather by rubbing hands together for 20 seconds, rinse with potable water.

Other information

EMERGENCY PHONE: 1-800-851-7145

See SDS MS0801277

FOR COMMERCIAL USE

See container for Lot Code and Expiry Date.

Store in a cool dry place.

Inactive ingredients

Water, Cocamidopropyl betaine, Cocamidopropyl PG-Dimmonium Chloride Phosphate, Laurtrimonium Chloride, PEG-6 Cocamide, Iodopropynyl Butylcarbamate, Methylisothiazolinone

Questions or comments?

1-800-558-2332 Monday through Friday 7:30 AM to 5:00 PM Central Standard Time

www.diversey.com

PACKAGE LABEL

Diversey

NDC 64536-1948-3

Soft Care Sentry

Foaming Antibacterial Hand Soap

For commercial use

NSF

Nonfood Compounds

Program Listed E2

Registration 156691

(L) Exp.

Net Contents

1.3 L / 1.37 U.S. Qt.

SKU: 101100320